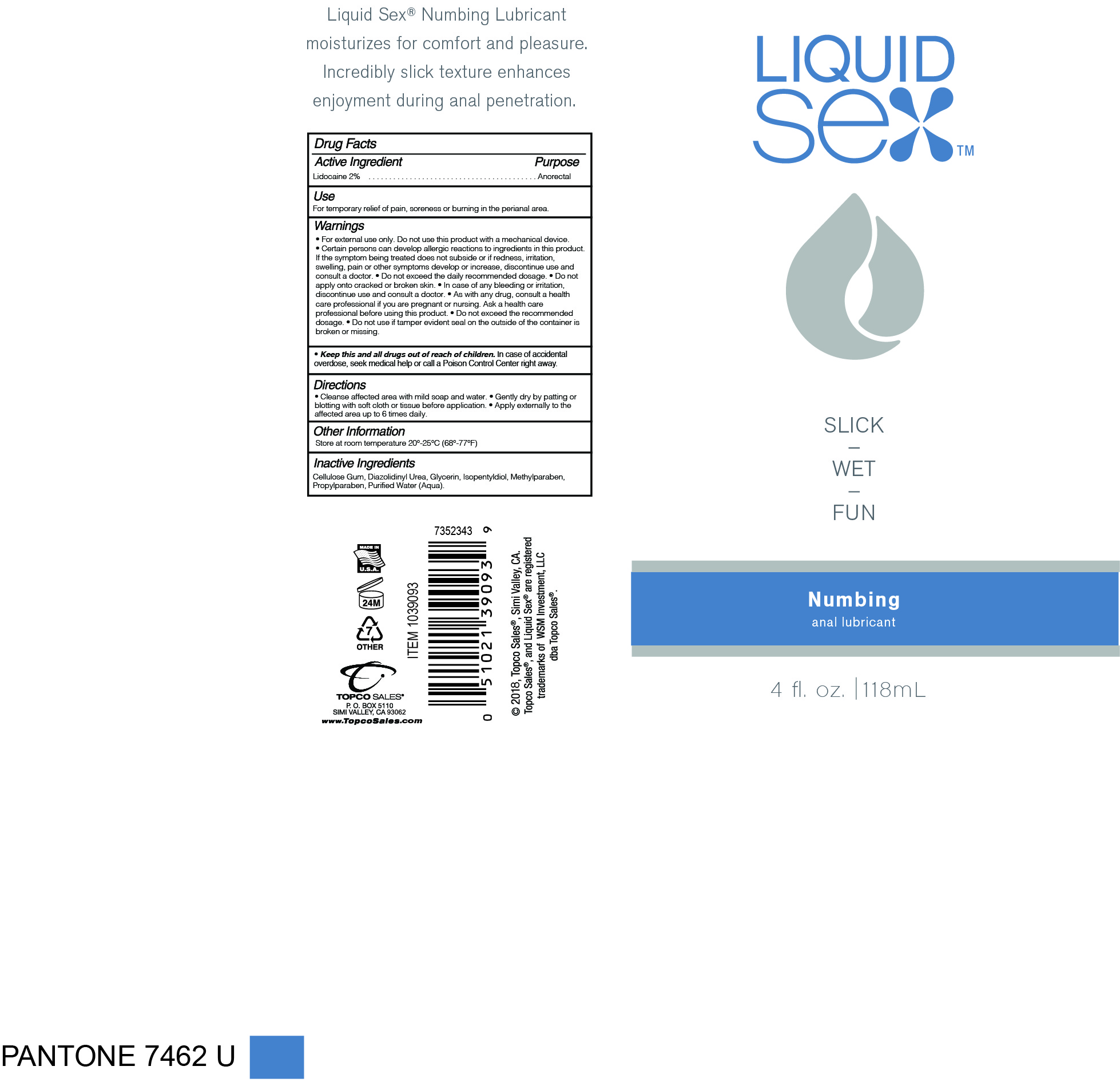 DRUG LABEL: Liquid Sex
NDC: 69797-101 | Form: GEL
Manufacturer: WSM Investment LLC. Topco Sales
Category: otc | Type: HUMAN OTC DRUG LABEL
Date: 20171214

ACTIVE INGREDIENTS: LIDOCAINE 2.36 g/118 mL
INACTIVE INGREDIENTS: DIAZOLIDINYL UREA; METHYLPARABEN; PROPYLENE GLYCOL; WATER; CARBOXYMETHYLCELLULOSE CALCIUM; PROPYLPARABEN; ISOPENTYLDIOL; GLYCERIN

ACTIVE INGREDIENT

Lidocaine 2%

PURPOSE

Anorectal

INDICATIONS AND USAGE

For temporary relief of pain, soreness or burning in the perianal area.

WARNINGS

- For external use only. Do not use product with a mechanical device.
- Certain persons can develop allergic reactions to ingredients in this product. If the symptoms being treated does not subside or if redness, irritation, swelling, pain or other symptoms develop or increase, discontinue use and consult a doctor.
- Do not exceed the daily recommended dosage.
- Do not apply onto cracked or broken skin.
- In case of any bleeding or irritation, discontinue use and consult a doctor.

KEEP OUT OF REACH OF CHILDREN

- Keep this and all drugs out of reach of children. In case of accidental overdose, seek medical help or call a Poison Control Center right away.
- As with any drug, consult a health care professional if you are pregnant or nursing. Ask a health care professional before using this product.
- Do not exceed recommended dosage.

DOSAGE AND ADMINISTRATION

- Cleanse affected area with mild soap and water. Gently dry by patting or blotting with toilet tissue or a soft cloth before application.
- Apply externally to the affected area up to 6 times daily.

OTHER SAFETY INFORMATION

- Store at room temperature 20° - 25°C (68°-77°F)
- Tamper-Evident: Do not use if tamper evident seal on the outside of the container is broken or missing.

INACTIVE INGREDIENT

Cellulose Gum, Diazolidinyl Urea, Glycerin, Isopentyldiol, Methylparaben, Propylparaben, Purified Water (Aqua).